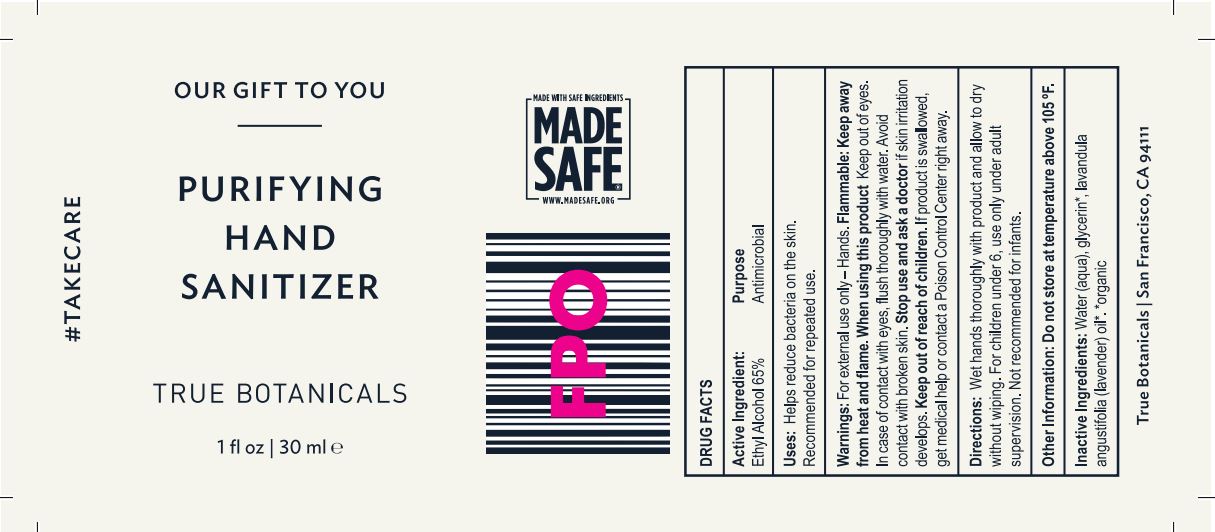 DRUG LABEL: Purifying Hand Sanitizer
NDC: 62742-4188 | Form: LIQUID
Manufacturer: Allure Labs Inc
Category: otc | Type: HUMAN OTC DRUG LABEL
Date: 20200428

ACTIVE INGREDIENTS: ALCOHOL 650 mg/1 mL
INACTIVE INGREDIENTS: WATER; GLYCERIN; LAVENDER OIL

DRUG FACTS

Active Ingredients:

Ethyl Alcohol - 65%

Purpose: Antimicrobial

INDICATIONS AND USAGE

Uses: Helps to reduce bacteria on skin. Recommended for repeated use.

WARNINGS

Warning: For External use only - Hands

Flammable: Keep away from heat and Flame.

When using this products:

- Keep out of eyes. In case of contact with eyes, flush thoroughly with water.
- Avoid contact with broken skin.

Stop use and ask a doctor if skin irritation develops.

Keep out of reach of children:

- If product is swallowed, get medical help or contact a Poison Control Center right away.

Directions:

- Wet hands throughly with product and allow to dry without wiping. For children under 6, use only under adult supervision. Not recommended for infants.

INACTIVE INGREDIENT

Inactive Ingredients: Water (Aqua), Glycerin, Lavandula angustifolia (lavender) oil.

PACKAGE LABEL

True Botanicals

San Francisco, CA 94111